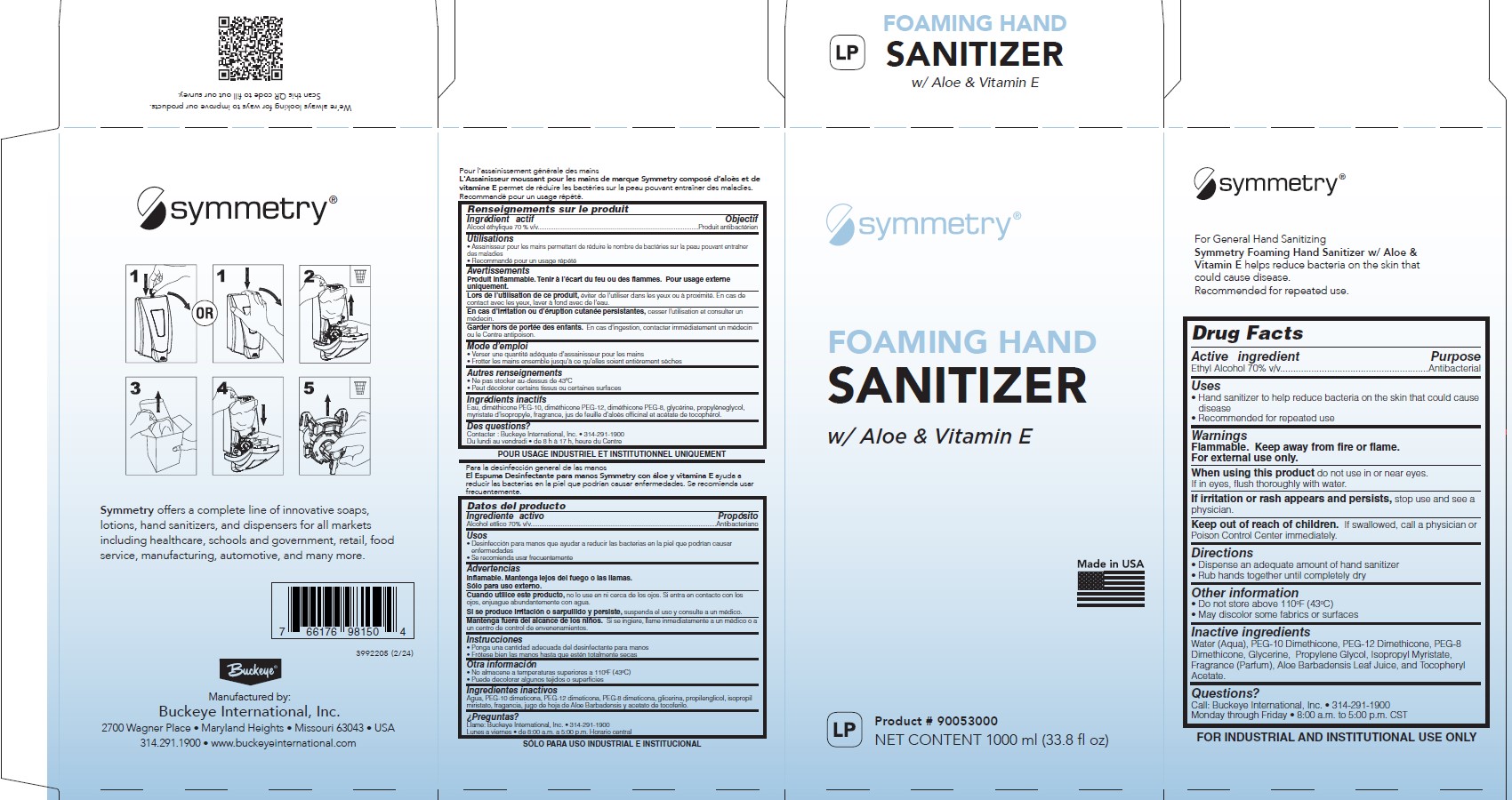 DRUG LABEL: Symmetry Foaming Hand Sanitizer
NDC: 30805-021 | Form: LIQUID
Manufacturer: Buckeye International, Inc.
Category: otc | Type: HUMAN OTC DRUG LABEL
Date: 20250327

ACTIVE INGREDIENTS: ALCOHOL 70 mL/100 mL
INACTIVE INGREDIENTS: PEG-10 DIMETHICONE (600 CST); ISOPROPYL MYRISTATE; ALOE; PEG-8 DIMETHICONE; .ALPHA.-TOCOPHEROL ACETATE; PROPYLENE GLYCOL; PEG-12 DIMETHICONE (300 CST); WATER; GLYCERIN

Drug Facts 30805-021

Active ingredient

Ethyl Alcohol 70% v/v

Purpose

Antibacterial

Warnings

Flammable. Keep away from fire or flame.

For external uses only.

When using this product do not use in or near eyes.

If in eyes, flush thoroughly with water.

STOP USE

If irritation or rash appears and persists, stop use and see a physician.

Keep out of reach of children. If swallowed, call a physician or Poison Control Center immediately.

Directions

- Dispense an adequate amount of hand sanitizer
- Rub Hands together until completely dry

Other information

- Do not store above 110°F (43°C)
- May discolor some fabrics or surfaces

Inactive ingredients

Water (Aqua), PEG-10 Dimethicone, PEG-12 Dimethicone, PEG-8 Dimethicone, Glycerine, Propylene Glycol, Isopropyl Myristate, Fragrance (Parfum). Aloe Barbadensis Leaf Juice, and Tocopheryl Acetate.

Questions?

Call: Buckeye International, Inc. • 314-291-1900

Monday through Friday • 8:00 a.m. to 5:00 p. m. CST

Uses

- Hand sanitizer to help reduce bacteria on the skin that could cause disease
- Recommended for repeated use

PACKAGE LABEL

symmetry

FOAMING HAND

SANITIZER

w/ Aloe &Vitamin E

Made in USA

LP Product # 9005300

NET CONTENTS 1000 ml (33.8 fl oz)